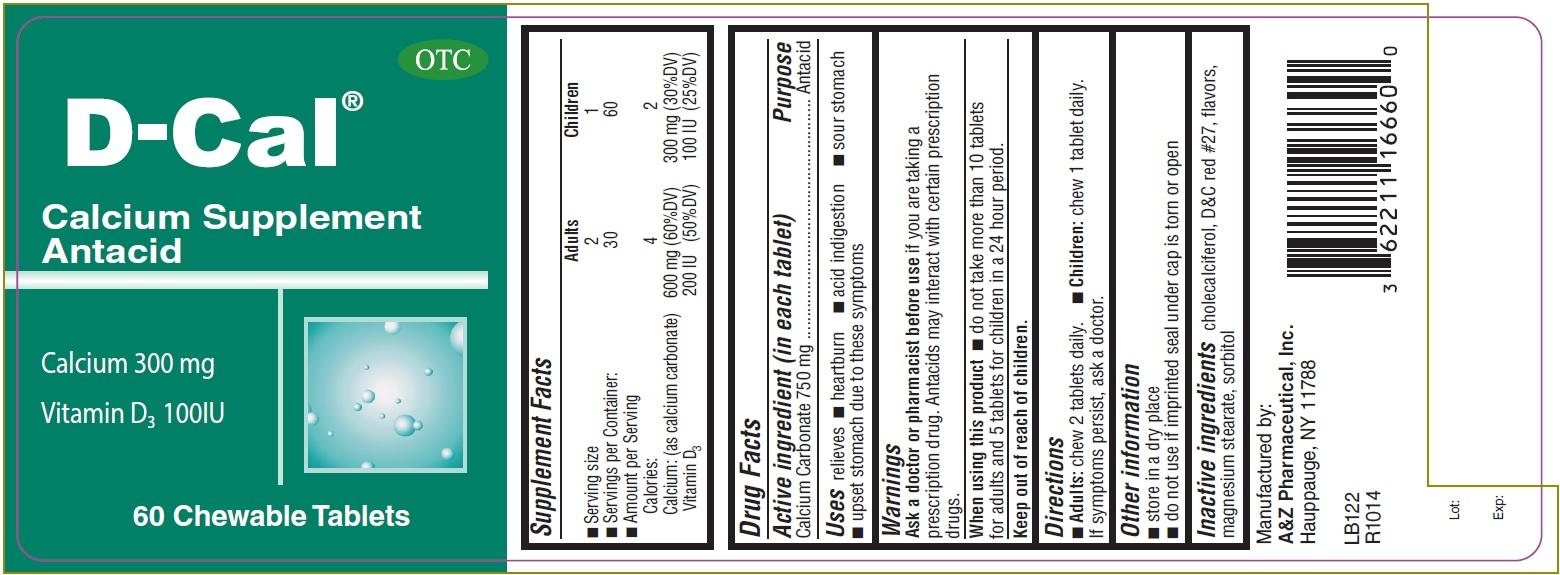 DRUG LABEL: D-CAL
NDC: 62211-166 | Form: TABLET, CHEWABLE
Manufacturer: A&Z Pharmaceutical Inc.
Category: otc | Type: HUMAN OTC DRUG LABEL
Date: 20250908

ACTIVE INGREDIENTS: CALCIUM CARBONATE 750 mg/1 1
INACTIVE INGREDIENTS: CHOLECALCIFEROL; D&C RED NO. 27; MAGNESIUM STEARATE; SORBITOL

D-CAL (calcium carbonate) tablet, chewable

Active ingredient (in each tablet)

Calcium Carbonate 750 mg

Purpose

Antacid

Uses

relieves

- heartburn
- acid indigestion
- sour stomach
- upset stomach due to these symptoms

Warnings

Ask a doctor or pharmacist before use if you are taking a prescription drug. Antacids may interact with certain prescription drugs.

When using this product

- do not take more than 10 tablets for adults and 5 tablets for children in a 24 hour period.

Directions

- Adults: chew 2 tablets daily.
- Children: chew 1 tablet daily. If symptoms persist, ask a doctor.

Other information

- Store in a dry place
- do not use if imprinted seal under cap is torn or open

Inactive ingredients

Cholecalciferol, D&C red #27, flavors, magnesium stearate, sorbitol